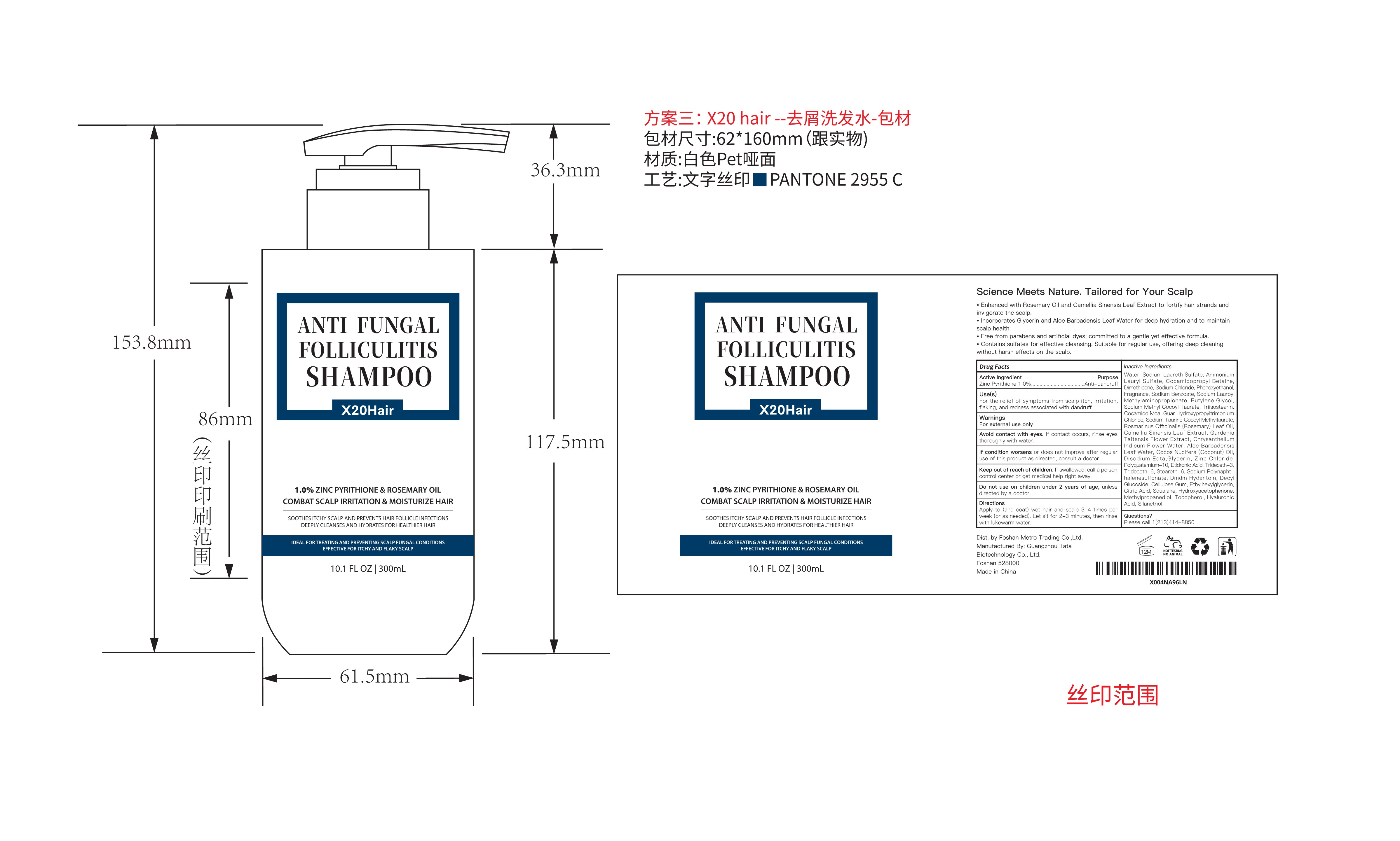 DRUG LABEL: X20HAIR ANTI FUNGALFOLLICULITISSHAMPOO
NDC: 84066-106 | Form: LIQUID
Manufacturer: Guangzhou Tata Biotechnology Co., Ltd.
Category: otc | Type: HUMAN OTC DRUG LABEL
Date: 20251222

ACTIVE INGREDIENTS: ZINC PYRITHIONE 1 mg/100 mL
INACTIVE INGREDIENTS: ROSEMARY OIL; TOCOPHEROL; ETIDRONIC ACID; SODIUM METHYL COCOYL TAURATE; COCAMIDOPROPYL BETAINE; PHENOXYETHANOL; SODIUM BENZOATE; GUAR HYDROXYPROPYLTRIMONIUM CHLORIDE; STEARETH-6; FORMALDEHYDE/SODIUM NAPHTHALENESULFONATE COPOLYMER (3000 MW); HYDROXYACETOPHENONE; SILANETRIOL; CHRYSANTHELLUM INDICUM FLOWER OIL; WATER; SODIUM LAURETH SULFATE; DIMETHICONE; BUTYLENE GLYCOL; TRIISOSTEARIN; FRAGRANCE LY-11285; SODIUM TAURINE COCOYL METHYLTAURATE; CAMELLIA SINENSIS LEAF; HYALURONIC ACID; CITRIC ACID; METHYLPROPANEDIOL; TRIDECETH-6; TRIDECETH-3; CELLULOSE GUM; ALOE VERA LEAF OIL; ZINC CHLORIDE; SODIUM LAUROYL METHYLAMINOPROPIONATE; SQUALANE; POLYQUATERNIUM-10 (400 CPS AT 2%); DMDM HYDANTOIN; DECYL GLUCOSIDE; EDETATE DISODIUM; GLYCERIN; ETHYLHEXYLGLYCERIN; COCOS NUCIFERA (COCONUT) OIL; GARDENIA TAITENSIS FLOWER; AMMONIUM LAURYL SULFATE; SODIUM CHLORIDE; COCAMIDE MEA

X20HAIR ANTI FUNGALFOLLICULITIS SHAMPOO

ACTIVE INGREDIENT

Zinc Pyrithione 1.0%

PURPOSE

Anti-dandruff

INDICATIONS AND USAGE

For the relief of symptoms from scalp itch, irritationflaking, and redness associated with dandruff.

WARNINGS

For external use only

WHEN USING

Avoid contact with eyes. lf contact occurs, rinse eyesthoroughly with water.

STOP USE

If condition worsens or does not improve after regularuse of this product as directed, consult a doctor.

Keep out of reach of children. lf swallowed, call a poisoncontrol center or get medical help right away.

Do not use on children under 2 years of age, unlessdirected by a doctor.

DOSAGE AND ADMINISTRATION

DirectionsApply to(and coat)wet hair and scalp 3-4 times perweek (or as needed).Let sit for 2-3 minutes, then rinsewith lukewarm water.

INACTIVE INGREDIENT

Water, Sodium Laureth Sulfate, AmmoniumLauryl Sulfate,Cocamidopropyl Betaine,Dimethicone, Sodium Chloride, Phenoxyethanol.Fragrance, Sodium Benzoate, Sodium LauroylMethylaminopropionate, Butylene Glycol,Sodium Methyl Cocoyl Taurate, Triisostearin,Cocamide Mea, Guar HydroxypropyltrimoniumChloride, Sodium Taurine Cocoyl Methyltaurate,Rosmarinus Ofhcinalis(Rosemary)Leaf Oil,Camellia Sinensis Leaf Extract, GardeniaTaitensis Flower Extract,ChrysanthellumIndicum Flower Water, Aloe BarbadensisLeaf Water, Cocos Nucifera(Coconut) Oil.Disodium Edta,Glycerin, Zinc ChloridePolyquaterium-10, Etidronic Acid, Trideceth-3,Trideceth-6,Steareth-6, Sodium Polynapht-halenesulfonate, Dmdm Hydantoin, Decy!Glucoside, Cellulose Gum, Ethylhexylglycerin,Citric Acid, Squalane, Hydroxyacetophenone,Methylpropanediol, Tocopherol, HyaluronicAcid, Silanetriol.

QUESTIONS

Please call 1(213)414-8850